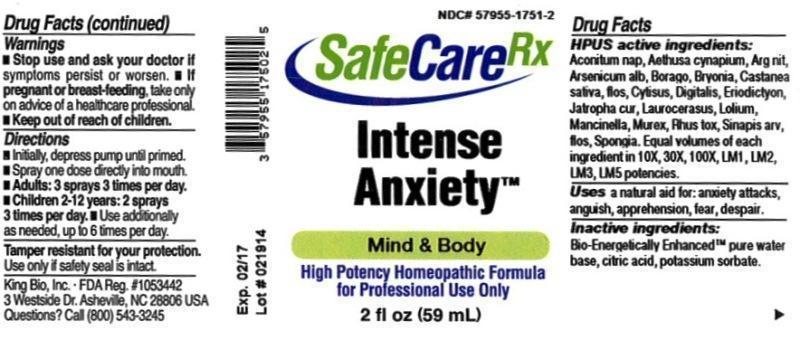 DRUG LABEL: Intense Anxiety
NDC: 57955-1751 | Form: LIQUID
Manufacturer: King Bio Inc.
Category: homeopathic | Type: HUMAN OTC DRUG LABEL
Date: 20140325

ACTIVE INGREDIENTS: ACONITUM NAPELLUS 10 [hp_X]/59 mL; AETHUSA CYNAPIUM 10 [hp_X]/59 mL; SILVER NITRATE 10 [hp_X]/59 mL; ARSENIC TRIOXIDE 10 [hp_X]/59 mL; BORAGE 10 [hp_X]/59 mL; BRYONIA ALBA ROOT 10 [hp_X]/59 mL; CASTANEA SATIVA FLOWER 10 [hp_X]/59 mL; CYTISUS SCOPARIUS FLOWERING TOP 10 [hp_X]/59 mL; DIGITALIS 10 [hp_X]/59 mL; ERIODICTYON CALIFORNICUM LEAF 10 [hp_X]/59 mL; JATROPHA CURCAS SEED 10 [hp_X]/59 mL; PRUNUS LAUROCERASUS LEAF 10 [hp_X]/59 mL; LOLIUM TEMULENTUM TOP 10 [hp_X]/59 mL; HIPPOMANE MANCINELLA FRUITING LEAFY TWIG 10 [hp_X]/59 mL; HEXAPLEX TRUNCULUS HYPOBRANCHIAL GLAND JUICE 10 [hp_X]/59 mL; TOXICODENDRON PUBESCENS LEAF 10 [hp_X]/59 mL; SINAPIS ARVENSIS FLOWERING/FRUITING TOP 10 [hp_X]/59 mL; SPONGIA OFFICINALIS SKELETON, ROASTED 10 [hp_X]/59 mL
INACTIVE INGREDIENTS: WATER; CITRIC ACID MONOHYDRATE; POTASSIUM SORBATE

Intense Anxiety™

ACTIVE INGREDIENT

Drug Facts__________________________________________________________________________________________________________

HPUS active ingredients: Aconitum napellus, Aethusa cynapium, Argentum nitricum, Arsenicum album, Borago officinalis, Bryonia, Castanea sativa, flos, Cytisus scoparius, Digitalis purpurea, Eriodictyon californicum, Jatropha curcas, Laurocerasus, Lolium temulentum, Mancinella, Murex purpurea, Rhus toxicodendron, Sinapis arvensis, flos, Spongia tosta. Equal volumes of each ingredient in 10X, 30X, 100X, LM1, LM2, LM3, LM5 potencies.

INDICATIONS AND USAGE

Uses a natural aid for: anxiety attacks, anguish, apprehension, fear, despair.

Inactive Ingredients:

Bio-Energetically Enhanced™ pure water, citric acid and potassium sorbate.

Warnings

- Stop use and ask your doctor if symptoms persist or worsen.
- If pregnant or breast-feeding, take only on advice of a healthcare professional.

- Keep out of reach of children

Directions

- Initially, depress pump until primed.
- Spray one dose directly into mouth.
- Adults: 3 sprays 3 times per day.
- Children 2-12 years: 2 sprays 3 times per day.
- Use additionally as needed, up to 6 times per day.

OTHER SAFETY INFORMATION

Tamper resistant for your protection. Use only if safety seal is intact.

PURPOSE

Uses a natural aid for:

- anxiety attacks
- anguish
- apprehension
- fear
- despair